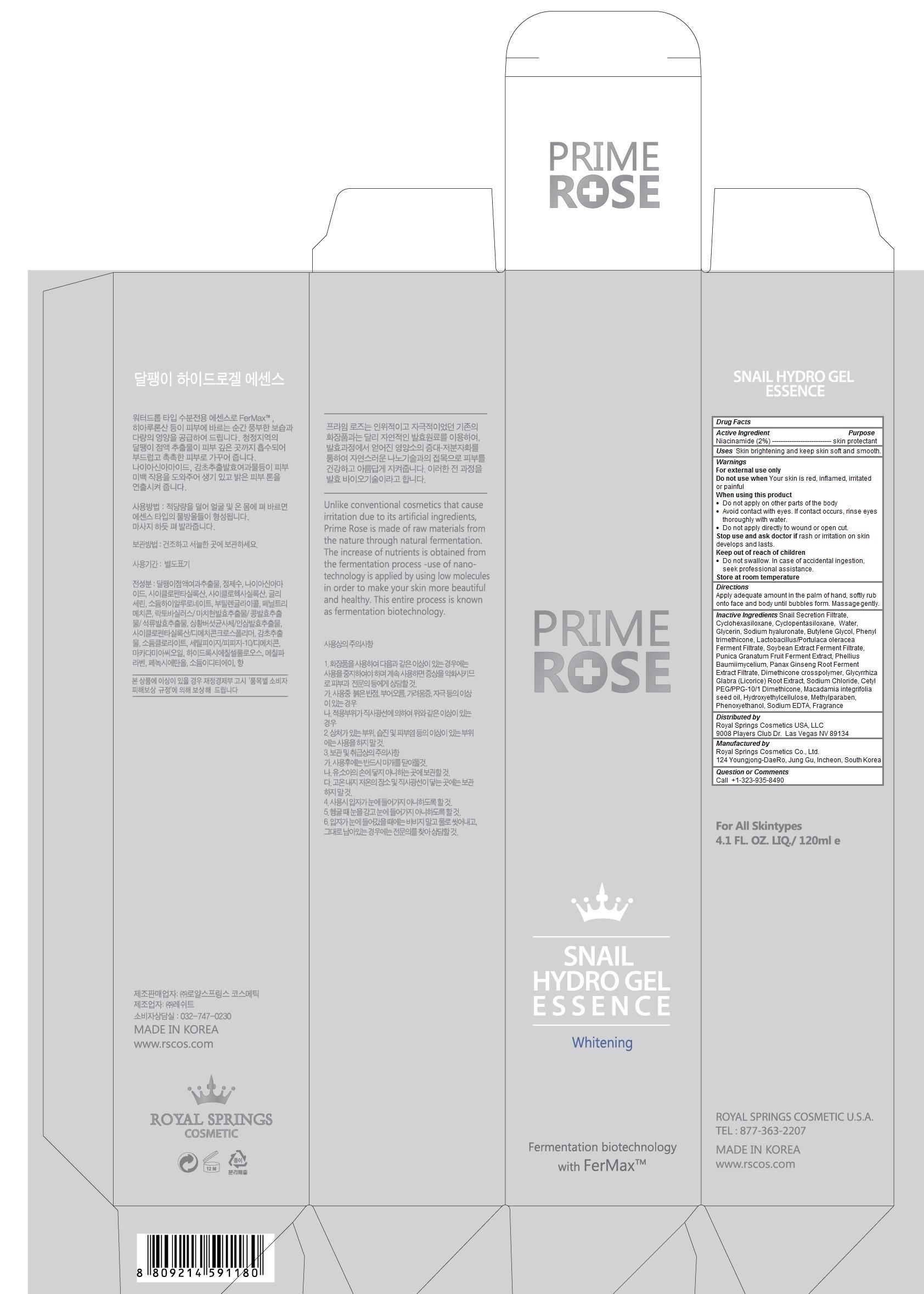 DRUG LABEL: PRIMEROSE SNAIL HYDRO ESSENCE
NDC: 69888-104 | Form: GEL
Manufacturer: Royal Springs Cosmetics USA, LLC
Category: otc | Type: HUMAN OTC DRUG LABEL
Date: 20190115

ACTIVE INGREDIENTS: NIACINAMIDE 0.02 1/120 mL
INACTIVE INGREDIENTS: SNAIL, UNSPECIFIED; CYCLOMETHICONE 6; CYCLOMETHICONE 5; WATER; GLYCERIN; HYALURONATE SODIUM; BUTYLENE GLYCOL; PHENYL TRIMETHICONE; POMEGRANATE; ASIAN GINSENG; DIMETHICONE CROSSPOLYMER (450000 MPA.S AT 12% IN CYCLOPENTASILOXANE); GLYCYRRHIZA GLABRA; SODIUM CHLORIDE; CETYL PEG/PPG-10/1 DIMETHICONE (HLB 3); MACADAMIA OIL; HYDROXYETHYL CELLULOSE (100 MPA.S AT 2%); METHYLPARABEN; PHENOXYETHANOL; EDETATE SODIUM

PRIMEROSE SNAIL HYDRO GEL ESSENCE

Active ingredient

Niacinamide (2%)

Purpose

skin protectant

Keep out of reach of children

- Do not swallow. In case of accidental ingestion, seek professional assistance.

Uses

Skin brightening and keep skin soft and smooth.

Warnings

For external use only
Do not use when Your skin is red, inflamed, irritated or painful
When using this product
- Do not apply on other parts of the body
- Avoid contact with eyes. If contact occurs, rinse eyes thoroughly with water.
- Do not apply directly to wound or open cut.
Stop use and ask doctor if rash or irritation on skin develops and lasts.
Store at room temperature

Directions

Apply adequate amount in the palm of hand, softly rub onto face and body until bubbles form. Massage gently.

Inactive ingredients

Snail Secretion Filtrate, Cyclohexasiloxane, Cyclopentasiloxane, Water, Glycerin, Sodium hyaluronate, Butylene Glycol, Phenyl trimethicone, Lactobacillus/Portulaca oleracea Ferment Filtrate, Soybean Extract Ferment Filtrate, Punica Granatum Fruit Ferment Extract, Phellius Baumiimycelium, Panax Ginseng Root Ferment Extract Filtrate, Dimethicone crosspolymer, Glycyrrhiza Glabra (Licorice) Root Extract, Sodium Chloride, Cetyl PEG/PPG-10/1 Dimethicone, Macadamia integrifolia seed oil, Hydroxyethylcellulose, Methylparaben, Phenoxyethanol, Sodium EDTA, Fragrance